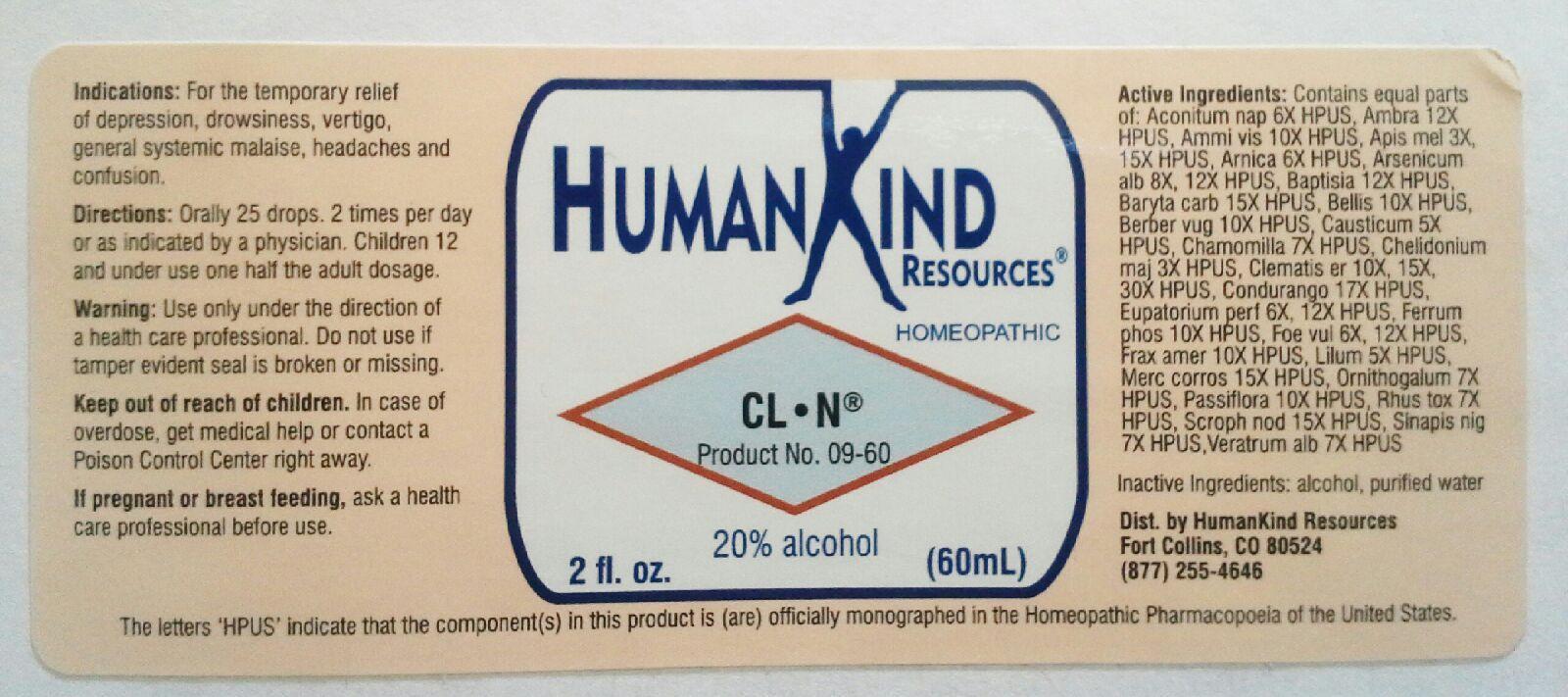 DRUG LABEL: CL-N
NDC: 64616-087 | Form: LIQUID
Manufacturer: Vitality Works, Inc.
Category: homeopathic | Type: HUMAN OTC DRUG LABEL
Date: 20251217

ACTIVE INGREDIENTS: ACONITUM NAPELLUS 6 [hp_X]/1 mL; AMBERGRIS 12 [hp_X]/1 mL; AMMI VISNAGA FRUIT 10 [hp_X]/1 mL; APIS MELLIFERA 15 [hp_X]/1 mL; ARNICA MONTANA 6 [hp_X]/1 mL; ARSENIC TRIOXIDE 12 [hp_X]/1 mL; BAPTISIA TINCTORIA ROOT 12 [hp_X]/1 mL; BARIUM CARBONATE 15 [hp_X]/1 mL; BELLIS PERENNIS 10 [hp_X]/1 mL; BERBERIS VULGARIS ROOT BARK 10 [hp_X]/1 mL; CAUSTICUM 5 [hp_X]/1 mL; MATRICARIA RECUTITA 7 [hp_X]/1 mL; CHELIDONIUM MAJUS 3 [hp_X]/1 mL; CLEMATIS RECTA FLOWERING TOP 30 [hp_X]/1 mL; MARSDENIA CONDURANGO BARK 17 [hp_X]/1 mL; EUPATORIUM PERFOLIATUM FLOWERING TOP 12 [hp_X]/1 mL; FERRUM PHOSPHORICUM 10 [hp_X]/1 mL; FENNEL SEED 12 [hp_X]/1 mL; FRAXINUS AMERICANA BARK 10 [hp_X]/1 mL; LILIUM LANCIFOLIUM WHOLE FLOWERING 5 [hp_X]/1 mL; MERCURIC CHLORIDE 15 [hp_X]/1 mL; ORNITHOGALUM UMBELLATUM 7 [hp_X]/1 mL; PASSIFLORA INCARNATA FLOWERING TOP 10 [hp_X]/1 mL; TOXICODENDRON PUBESCENS LEAF 7 [hp_X]/1 mL; SCROPHULARIA NODOSA 15 [hp_X]/1 mL; BLACK MUSTARD SEED 7 [hp_X]/1 mL; VERATRUM ALBUM ROOT 7 [hp_X]/1 mL
INACTIVE INGREDIENTS: WATER; ALCOHOL

CL-N

CL-N

Aconitum Napellus 6X Berberis Vuylgaris 10X Fraxinus Americana 10X
Ambra Grisea 12X Causticum 5X Lilium Tigrinum 5X
Ammi Visnaga 10X Chamomilla 7X Mercurius Corrosivus 15X
Apis Mellifica 3X, 15X Chilidonium Majus 3X Ornithogalum Umbellatum 7X
Arnica Montana 6X Clematis Erecta 10X, 15X, 30X Passiblora Incarnata 10X
Arsenicum Album 8X, 12X Condurango 17X Rhus Toxicodendron 7X
Baptisia Tinctoria 12X Eupatorium Perfoliatum 6X, 12X Scrophularia Nodosa 15X
Baryta Carbonica 15X Ferrum Phosphoricum 10X Sinapsis Nigra 7X
Bellis Perennis 10X Foeniculum Vulgare 6X, 12X Veratum Album 7X

CL-N

Alcohol, Purified Water

CL-N

Use only under the direction of a health care professional. Do not use if tamper evident seal is broken or missing.

CL-N

Keep out of reach of children. In case of overdose, get meidcal help or contact a Poison Control Center right away.

CL-N

For the temporory relief of depression, drowsiness, vertigo, general systemic malaise, headaches and confusion.

CL-N

Orally 25 drops, 2 times per day or as indicated by a physician. Children 12 and under use one half the adult dosage.

CL-N

Eases depression, drowsiness, vertigo, malaise, headaches and confusion.